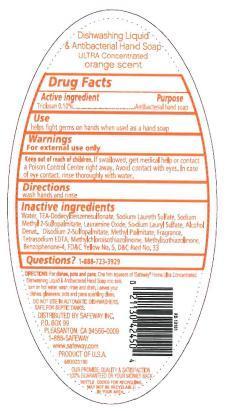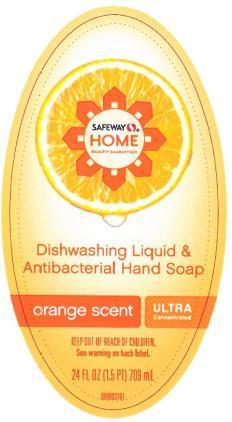 DRUG LABEL: Safeway Home Orange Scent
NDC: 63691-010 | Form: SOAP
Manufacturer: Sun Products Corporation
Category: otc | Type: HUMAN OTC DRUG LABEL
Date: 20151223

ACTIVE INGREDIENTS: TRICLOSAN 0.1 g/100 mL
INACTIVE INGREDIENTS: WATER; TRIETHANOLAMINE DODECYLBENZENESULFONATE; SODIUM LAURYL SULFATE; SODIUM LAURETH SULFATE; ALCOHOL; LAURAMINE OXIDE; DISODIUM 2-SULFOPALMITATE; METHYL PALMITATE; EDETATE SODIUM; METHYLCHLOROISOTHIAZOLINONE; METHYLISOTHIAZOLINONE; SULISOBENZONE; FD&C YELLOW NO. 5; D&C RED NO. 33

Active ingredient

Triclosan 0.10%

INDICATIONS AND USAGE

Use helps fight germs on hands when used as a hand soap

WARNINGS

For external use only

Keep out of reach of children. If swallowed, get medical help or contact a Poison Control Center right away. In case of eye contact, rinse thoroughly with water.

DOSAGE AND ADMINISTRATION

Directions wash hands and rinse

PURPOSE

Antibacterial hand soap

INACTIVE INGREDIENT

Inactive ingredients Water, TEA-Dodecylbenzenesulfonate, Sodium Laureth Sulfate, Sodium Methyl 2-Sulfopalmitate, Lauramine Oxide, Sodium Lauryl Sulfate, Alcohol Denat., Disodium 2-Sulfopalmitate, Methyl Palmitate, Fragrance, Tetrasodium EDTA, Methylchloroisothiazolinone, Methylisothiazolinone, Benzophenone-4, Yellow No. 5, Red No. 33

Questions? 1-888-723-3929

PACKAGE LABEL

LBLFR

LBLBK